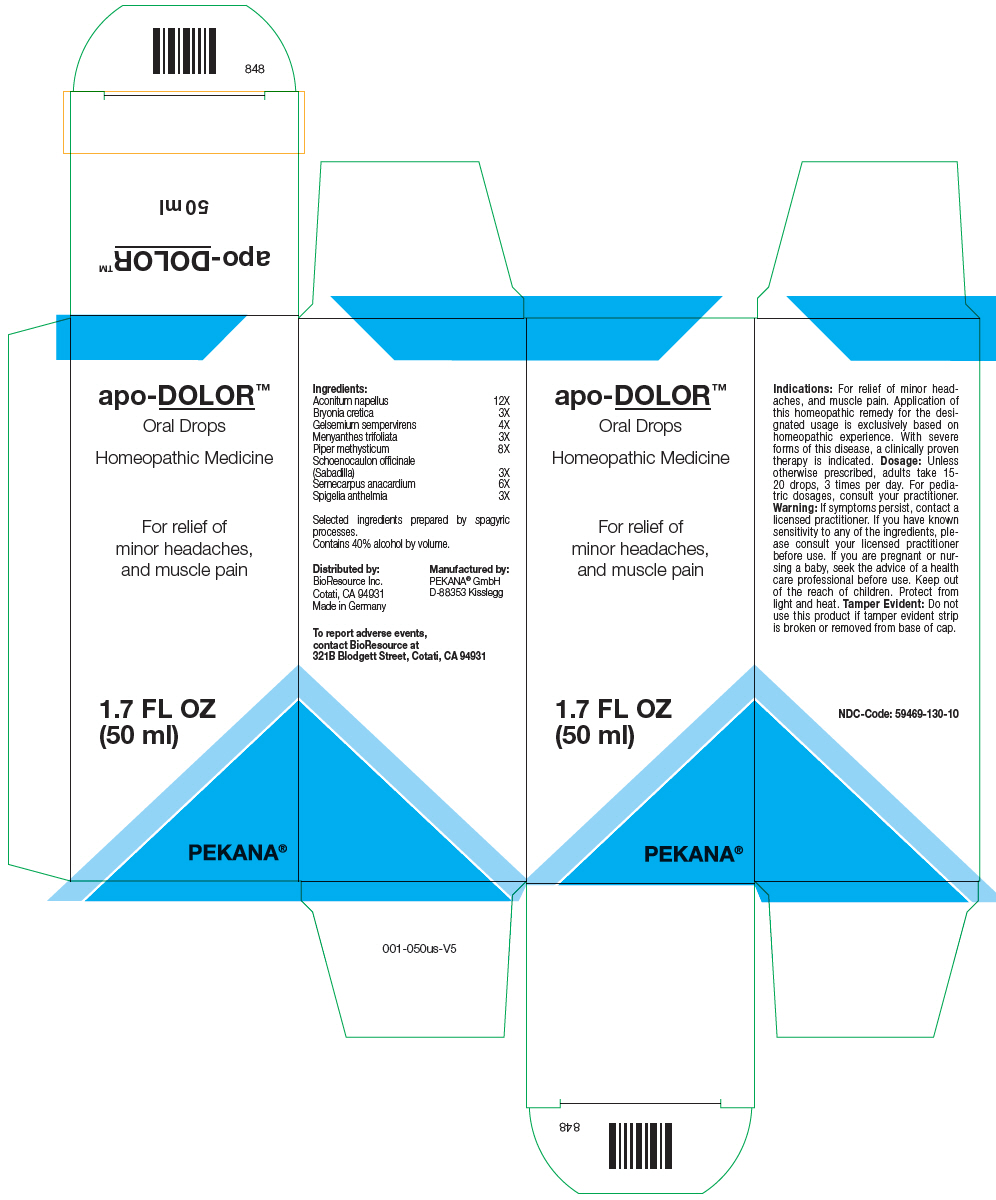 DRUG LABEL: apo-DOLOR
NDC: 59469-130 | Form: SOLUTION/ DROPS
Manufacturer: PEKANA Naturheilmittel GmbH
Category: homeopathic | Type: HUMAN OTC DRUG LABEL
Date: 20221202

ACTIVE INGREDIENTS: ACONITUM NAPELLUS WHOLE 12 [hp_X]/50 mL; Semecarpus anacardium Fruit 6 [hp_X]/50 mL; Bryonia Dioica Root 3 [hp_X]/50 mL; Gelsemium sempervirens Root 4 [hp_X]/50 mL; MENYANTHES TRIFOLIATA WHOLE 3 [hp_X]/50 mL; Macropiper Methysticum Root 8 [hp_X]/50 mL; Schoenocaulon officinale Seed 3 [hp_X]/50 mL; SPIGELIA ANTHELMIA WHOLE 3 [hp_X]/50 mL
INACTIVE INGREDIENTS: Water; Alcohol

apo-DOLOR™

ACTIVE INGREDIENT

Ingredients:
Aconitum napellus | 12X
Bryonia cretica | 3X
Gelsemium sempervirens | 4X
Menyanthes trifoliata | 3X
Piper methysticum | 8X
Schoenocaulon officinale (Sabadilla) | 3X
Semecarpus anacardium | 6X
Spigelia anthelmia | 3X

Selected ingredients prepared by spagyric processes.

INACTIVE INGREDIENT

Contains 40% alcohol by volume.

Indications

PURPOSE

For relief of minor headaches, and muscle pain. Application of this homeopathic remedy for the designated usage is exclusively based on homeopathic experience. With severe forms of this disease, a clinically proven therapy is indicated.

Dosage

Unless otherwise prescribed, adults take 15-20 drops, 3 times per day. For pediatric dosages, consult your practitioner.

Warning

If symptoms persist, contact a licensed practitioner. If you have known sensitivity to any of the ingredients, please consult your licensed practitioner before use. If you are pregnant or nursing a baby, seek the advice of a health care professional before use.

Keep out of the reach of children.

Protect from light and heat.

Tamper Evident

Do not use this product if tamper evident strip is broken or removed from base of cap.

QUESTIONS

To report adverse events, contact BioResource at 321B Blodgett Street, Cotati, CA 94931

Distributed by:
BioResource Inc.
Cotati, CA 94931

Manufactured by:
PEKANA® GmbH
D-88353 Kisslegg

PRINCIPAL DISPLAY PANEL - 50 ml Bottle Box

apo-DOLOR™

Oral Drops

Homeopathic Medicine

For relief of
minor headaches,
and muscle pain

1.7 FL OZ
(50 ml)

PEKANA®